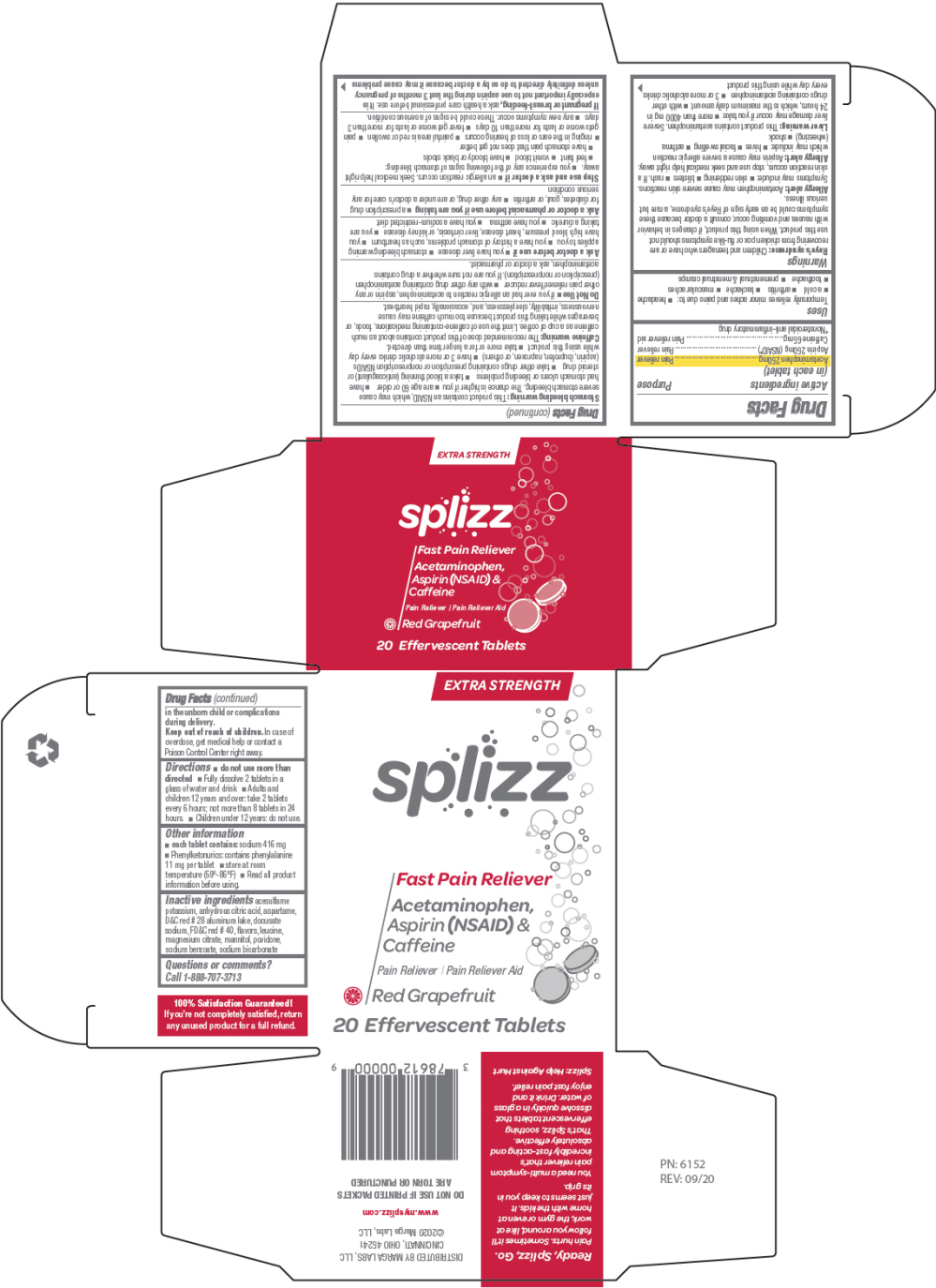 DRUG LABEL: Splizz Pain Reliever - Grapefruit-flavored
NDC: 78612-100 | Form: TABLET, EFFERVESCENT
Manufacturer: Marga Labs, LLC
Category: otc | Type: HUMAN OTC DRUG LABEL
Date: 20210125

ACTIVE INGREDIENTS: Acetaminophen 250 mg/1 1; Aspirin 250 mg/1 1; Caffeine 65 mg/1 1
INACTIVE INGREDIENTS: Citric Acid Monohydrate; Sodium bicarbonate; Mannitol; Povidone, Unspecified; Acesulfame potassium; Aspartame

Splizz Pain Reliever - Grapefruit-flavored Tablets

Drug Facts

ACTIVE INGREDIENT

Active ingredients (in each tablet) | Purpose
Acetaminophen 250mg | Pain reliever
Aspirin 250mg (NSAID [Nonsteroidal anti-inflammatory drug]) | Pain reliever
Caffeine 65mg | Pain reliever aid

Uses

Temporarily relieves minor aches and pains due to:

- headache
- a cold
- arthritis
- backache
- muscular aches
- toothache
- premenstrual & menstrual cramps

Warnings

Reye's syndrome

Children and teenagers who have or are recovering from chicken pox or flu-like symptoms should not use this product. When using this product, if changes in behavior with nausea and vomiting occur, consult a doctor because these symptoms could be an early sign of Reye's syndrome, a rare but serious illness.

Allergy alert

Acetaminophen may cause severe skin reactions. Symptoms may include:

- skin reddening
- blisters
- rash. If a skin reaction occurs, stop use and seek medical help right away.

Allergy alert

Aspirin may cause a severe allergic reaction which may include:

- hives
- facial swelling
- asthma (wheezing)
- shock

Liver warning

This product contains acetaminophen. Severe liver damage may occur if you take:

- more than 4000 mg in 24 hours, which is the maximum daily amount
- with other drugs containing acetaminophen
- 3 or more alcoholic drinks every day while using this product

Stomach bleeding warning

This product contains an NSAID, which may cause severe stomach bleeding. The chance is higher if you

- are age 60 or older
- have had stomach ulcers or bleeding problems
- take a blood thinning (anticoagulant) or steroid drug
- take other drugs containing prescription or nonprescription NSAIDs (aspirin, ibuprofen, naproxen, or others)
- have 3 or more alcoholic drinks every day while using this product
- take more or for a longer time than directed.

Caffeine warning

The recommended dose of this product contains about as much caffeine as a cup of coffee. Limit the use of caffeine-containing medications, foods, or beverages while taking this product because too much caffeine may cause nervousness, irritability, sleeplessness, and, occasionally, rapid heartbeat.

Do Not Use

- if you ever had an allergic reaction to acetaminophen, aspirin or any other pain reliever/fever reducer
- with any other drug containing acetaminophen (prescription or nonprescription). If you are not sure whether a drug contains acetaminophen, ask a doctor or pharmacist.

Ask a doctor before use if

- you have liver disease
- stomach bleeding warning applies to you
- you have a history of stomach problems, such as heartburn
- you have high blood pressure, heart disease, liver cirrhosis, or kidney disease
- you are taking a diuretic
- you have asthma
- you have a sodium-restricted diet

Ask a doctor or pharmacist before use if you are taking

- a prescription drug for diabetes, gout, or arthritis
- any other drug, or are under a doctor's care for any serious condition

Stop use and ask a doctor if

- an allergic reaction occurs. Seek medical help right away.
- you experience any of the following signs of stomach bleeding:
  - feel faint
  - vomit blood
  - have bloody or black stools
  - have stomach pain that does not get better
- ringing in the ears or loss of hearing occurs
- painful area is red or swollen
- pain gets worse or lasts for more than 10 days
- fever get worse or lasts for more than 3 days
- any new symptoms occur. These could be signs of a serious condition.

PREGNANCY OR BREAST FEEDING

If pregnant or breast-feeding, ask a health care professional before use. It is especially important not to use aspirin during the last 3 months of pregnancy unless definitely directed to do so by a doctor because it may cause problems in the unborn child or complications during delivery.

Keep out of reach of children. In case of overdose, get medical help or contact a Poison Control Center right away.

Directions

- do not use more than directed
- Fully dissolve 2 tablets in a glass of water and drink
- Adults and children 12 years and over: take 2 tablets every 6 hours; not more than 8 tablets in 24 hours.
- Children under 12 years: do not use.

Other information

- each tablet contains: sodium 416 mg
- Phenylketonurics: contains phenylalanine 11 mg per tablet
- store at room temperature (59°-86°F)
- Read all product information before using.

Inactive ingredients

acesulfame potassium, anhydrous citric acid, aspartame, D&C red # 28 aluminum lake, docusate sodium, FD&C red # 40, flavors, leucine, magnesium citrate, mannitol, povidone, sodium benzoate, sodium bicarbonate

Questions or comments?

Call 1-888-707-3713

DISTRIBUTED BY MARGA LABS, LLC
CINCINNATI, OHIO 45241

PRINCIPAL DISPLAY PANEL - 20 Tablet Pouch Carton

EXTRA STRENGTH

splizz

Fast Pain Reliever

Acetaminophen,
Aspirin (NSAID) &
Caffeine

Pain Reliever | Pain Reliever Aid

Red Grapefruit

20 Effervescent Tablets